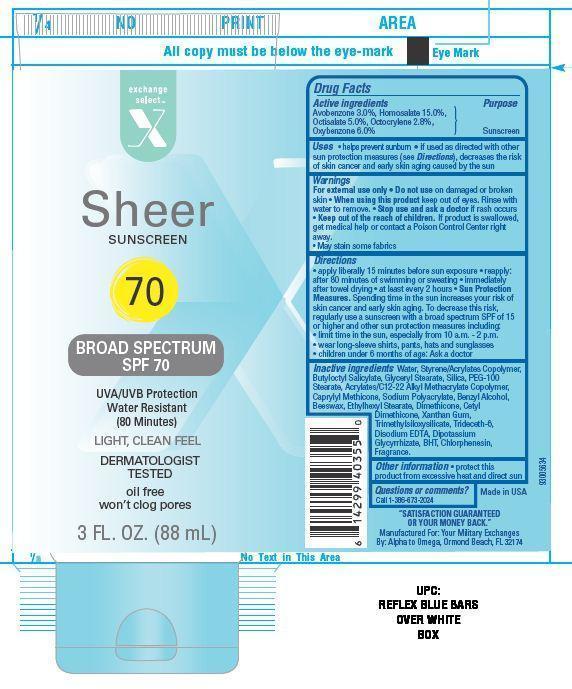 DRUG LABEL: Exchange Select Sheer Dry Touch Sunscreen
NDC: 55301-012 | Form: LOTION
Manufacturer: ARMY AND AIR FORCE EXCHANGE SERVICE
Category: otc | Type: HUMAN OTC DRUG LABEL
Date: 20131021

ACTIVE INGREDIENTS: AVOBENZONE 3 g/100 g; HOMOSALATE 15 g/100 g; OCTISALATE 5 g/100 g; OCTOCRYLENE 2.8 g/100 g; OXYBENZONE 6 g/100 g
INACTIVE INGREDIENTS: WATER; BUTYLOCTYL SALICYLATE; SILICON DIOXIDE; GLYCERYL MONOSTEARATE; PEG-100 STEARATE; CAPRYLYL TRISILOXANE; BENZYL ALCOHOL ; YELLOW WAX; ETHYLHEXYL STEARATE; DIMETHICONE; XANTHAN GUM; TETRASILANE; TRIDECETH-6; EDETATE DISODIUM; BUTYLATED HYDROXYTOLUENE; GLYCYRRHIZINATE DIPOTASSIUM; CHLORPHENESIN

Drug Facts:

Active Ingredients

Avobenzone 3.0 %

Homosalate 15.0%

Octisalate 5.0%

Octocrylene 2.8%

Oxybenzone 6.0%

Purpose

Sunscreen

Uses

- helps prevent sunburn
- If used as directed with other sun protection measures(see Directions), decreases the risk of skin cancer and early skin

Warnings

For external use only. Do not use on damaged or broken skin.

When using this product

- keep out of eyes. Rinse with water to remove.

Stop use and ask a doctor if

- rash occurs.

Keep out of reach of children.

If swallowed, get medical help or contact a Poison Control Center right away.

- May stain some fabrics

Directions

- apply liberally 15 minutes before sun exposure
- reapply:
- after 80 minutes of swimming or sweating
- immediately after towel drying
- at least every 2 hours
- Sun Protection Measures. Spending time in the sun increases your risk of skin cancer and early skin aging. To decrease this risk,regularly use a sunscreen with a broad spectrum SPF of 15 or higher and other sun protection measures including:
- limit time in the sun, especially from 10 a.m. - 2 p.m.
- wear long-sleeve shirts, pants,hats and sunglasses
- children under 6 months of age: Ask a doctor

Other information

- protect this product from excessive heat and direct sun

Inactive ingredients

Water, Styrene/Acrylates Copolymer, Butyloctyl Salicylate, Glyceryl Stearate, Silica, PEG-100 Stearate, Acrylates/C12-22 Alkyl Methacrylate Copolymer, Caprylyl Methicone, Sodium Polyacrylate, Benzyl Alcohol, Beeswax, Ethylhexyl Stearate, Dimethicone, Cetyl Dimethicone, Xanthan Gum, Trimethylsiloxysilicate, Trideceth-6, Disodium EDTA, Dipotassium Glycyrrhizate, BHT, Chlorphenesin, Fragrance.

Principal Display Panel

exchange

select

X

Sheer

SUNSCREEN

70

BROAD SPECTRUM SPF 70

UVA/UVB PROTECTION

Water Resistant

(80 Minutes)

LIGHT, CLEAN FEEL

DERMATOLOGIST

TESTED

oil free

won't clog pores

3 FL.OZ. (88 mL)

Questions or comments?

Call 1-396-673-2024